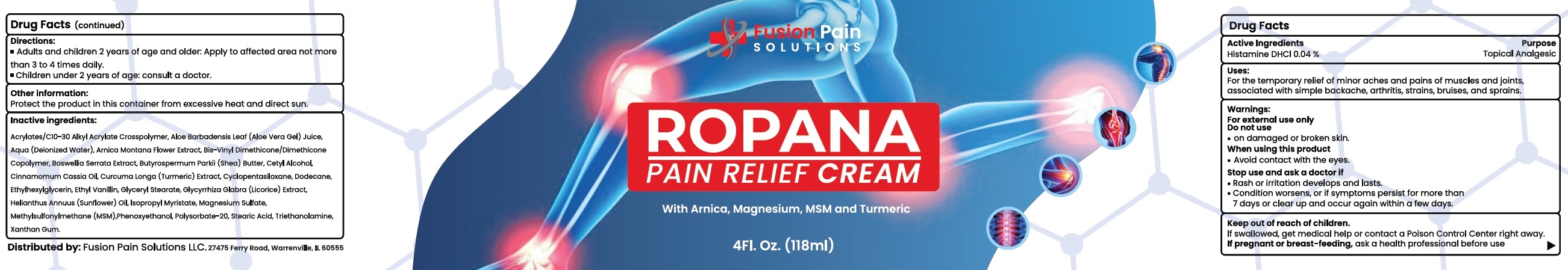 DRUG LABEL: ROPANA Pain Relief Cream
NDC: 83613-411 | Form: CREAM
Manufacturer: FUSION PAIN SOLUTIONS LLC
Category: otc | Type: HUMAN OTC DRUG LABEL
Date: 20231106

ACTIVE INGREDIENTS: HISTAMINE DIHYDROCHLORIDE 0.4 mg/1 mL
INACTIVE INGREDIENTS: ALOE VERA LEAF; WATER; ARNICA MONTANA FLOWER; INDIAN FRANKINCENSE; SHEA BUTTER; CETYL ALCOHOL; CYCLOMETHICONE 5; DODECANE; ETHYLHEXYLGLYCERIN; CHINESE CINNAMON OIL; TURMERIC; ETHYL VANILLIN; GLYCERYL MONOSTEARATE; GLYCYRRHIZA GLABRA; HELIANTHUS ANNUUS FLOWERING TOP; ISOPROPYL MYRISTATE; MAGNESIUM SULFATE, UNSPECIFIED FORM; DIMETHYL SULFONE; PHENOXYETHANOL; POLYSORBATE 20; STEARIC ACID; TROLAMINE; XANTHAN GUM

ROPANA Pain Relief Cream

Active Ingredients

Histamine DHCl 0.04%

Purpose

Topical Analgesic

Uses:

For the temporary relief of minor aches and pains of muscles and joints, associated with simple backache, arthritis, strains, bruises, and sprains.

Warnings:

For external use only

Do not use

- on damaged or broken skin.

When using this product

- Avoid contact with the eyes.

Stop use and ask a doctor if

- Rash or irritation develops and lasts.
- Condition worsens, or if symptoms persist for more than 7 days or clear up and occur again within a few days.

Keep out of reach of children.

If swallowed, get medical help or contact a Poison Control Center right away.

If pregnant or breast-feeding,

ask a health professional before use

Directions:

- Adults and children 2 years of age and older: Apply to affected area not more than 3 to 4 times daily.
- Chldren under 2 years of age: consult a doctor.

Other Information:

Protct the product in this container from excessive heat and direct sun.

Inactive ingredients:

Acrylates/C10-30 Alkyl Acrylate Crosspolymer, Aloe Barbadensis Leaf (Aloe Vera Gel) Juice, Aqua (Deionized Water), Arnica Montana Flower Extract, Bis-Vinyl Dimethicone/Dimethicone Copolymer, Boswellia Serrata Extract, Butyrospermum Parkii (Shea) Butter, Cetyl Alcohol, Cinnamomum Cassia Oil, Curcuma Longa (Turmeric) Extract, Cyclopentasiloxane, Dodecane, Ethylhexylglycerin, Ethyl Vanillin, Glyceryl Stearate, Glycyrrhiza Glaba (Licorice) Extract, Helianthus Annuus (Sunflower) Oil, Isopropyl Myristate, Magnesium Sulfate, Methylsulfonylmethane (MSM), Phenoxyethanol, Polysorbate-20, Stearic Acid, Triethanolamine, Xanthan Gum.